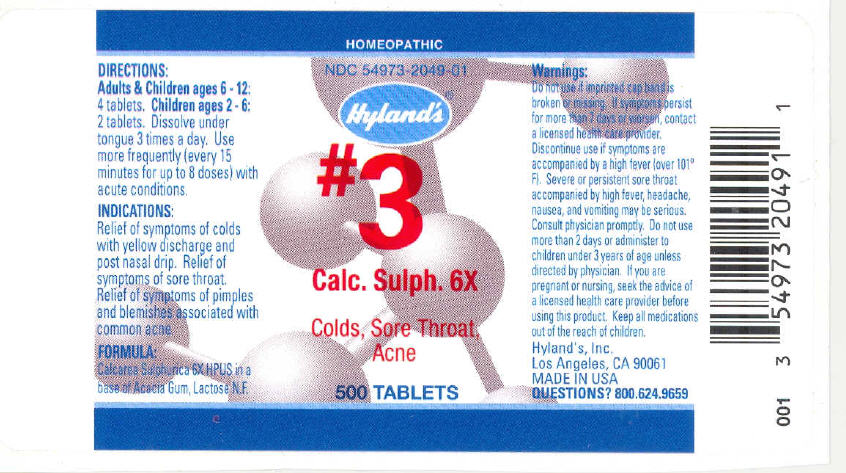 DRUG LABEL: CALCIUM SULPHATE
NDC: 54973-2049 | Form: TABLET
Manufacturer: Hyland's Inc.
Category: homeopathic | Type: HUMAN OTC DRUG LABEL
Date: 20221207

ACTIVE INGREDIENTS: CALCIUM SULFATE 6 [hp_X]/1 1
INACTIVE INGREDIENTS: LACTOSE; ACACIA

CALCIUM SULPHATE

DIRECTIONS

Adults & Children ages 6 - 12: 4 tablets. Children ages 2 - 6: 2 tablets. Dissolve under tongue 3 times a day. Use more frequently (every 15 minutes for up to 8 doses) with acute conditions.

PURPOSE

INDICATIONS

Relief of symptoms of colds with yellow discharge and post nasal drip. Relief of symptoms of sore throat. Relief of symptoms of pimples and blemishes associated with common acne.

ACTIVE INGREDIENT

FORMULA

Calcarea Sulphurica 6X HPUS in a base of Acacia Gum, Lactose N.F.

WARNINGS

Do not use if imprinted cap band is broken or missing.

ASK DOCTOR/PHARMACIST

If symptoms persist for more than 7 days or worsen, contact a licensed health care provider.

STOP USE

Discontinue use if symptoms are accompanied by a high fever (over 101°F).

ASK DOCTOR

Severe or persistent sore throat accompanied by high fever, headache, nausea, and vomiting may be serious. Consult physician promptly.

Do not use more than 2 days or administer to children under 3 years of age unless directed by physician.

PREGNANCY OR BREAST FEEDING

If you are pregnant or nursing, seek the advice of a licensed health care provider before using this product.

KEEP OUT OF REACH OF CHILDREN

Keep all medications out of the reach of children.

QUESTIONS?

800.624.9659

PRINCIPAL DISPLAY PANEL - 500 Tablet Bottle Label

HOMEOPATHIC

NDC 54973-2049-01

Hyland's®

#3

Calc. Sulph. 6X

Colds, Sore Throat,
Acne

500 TABLETS